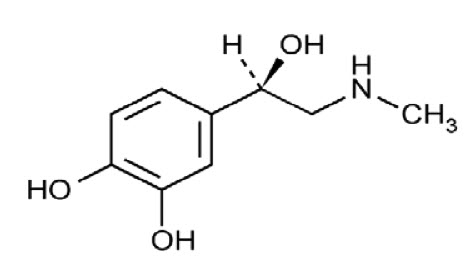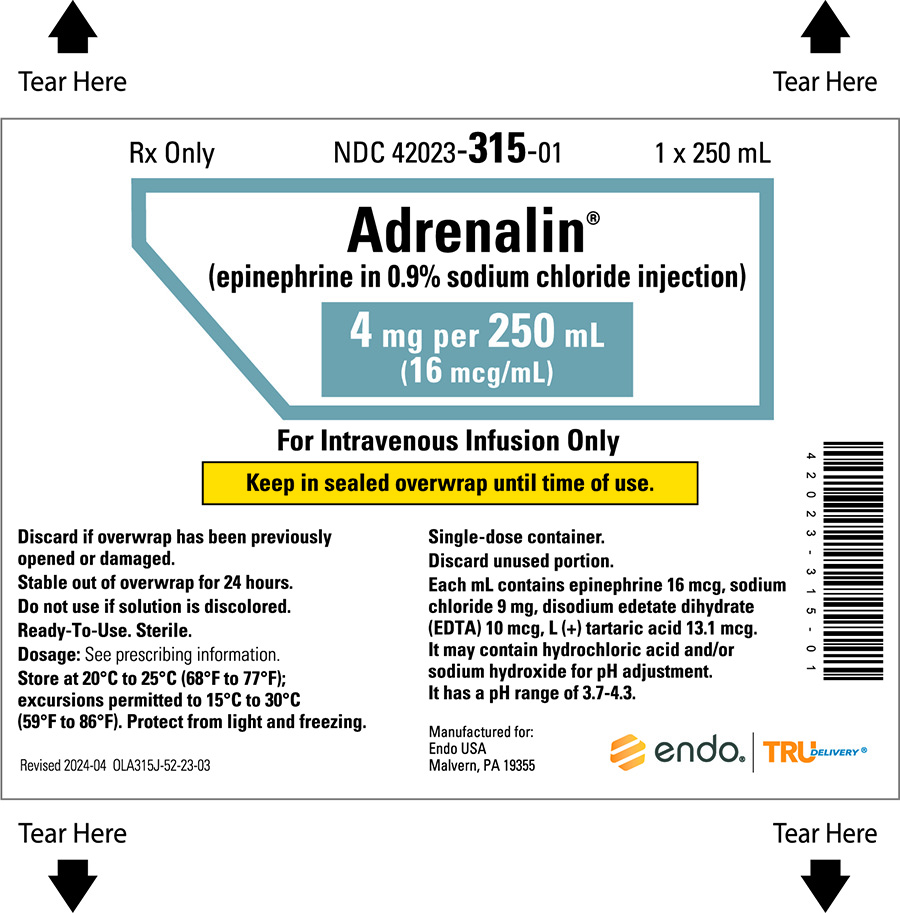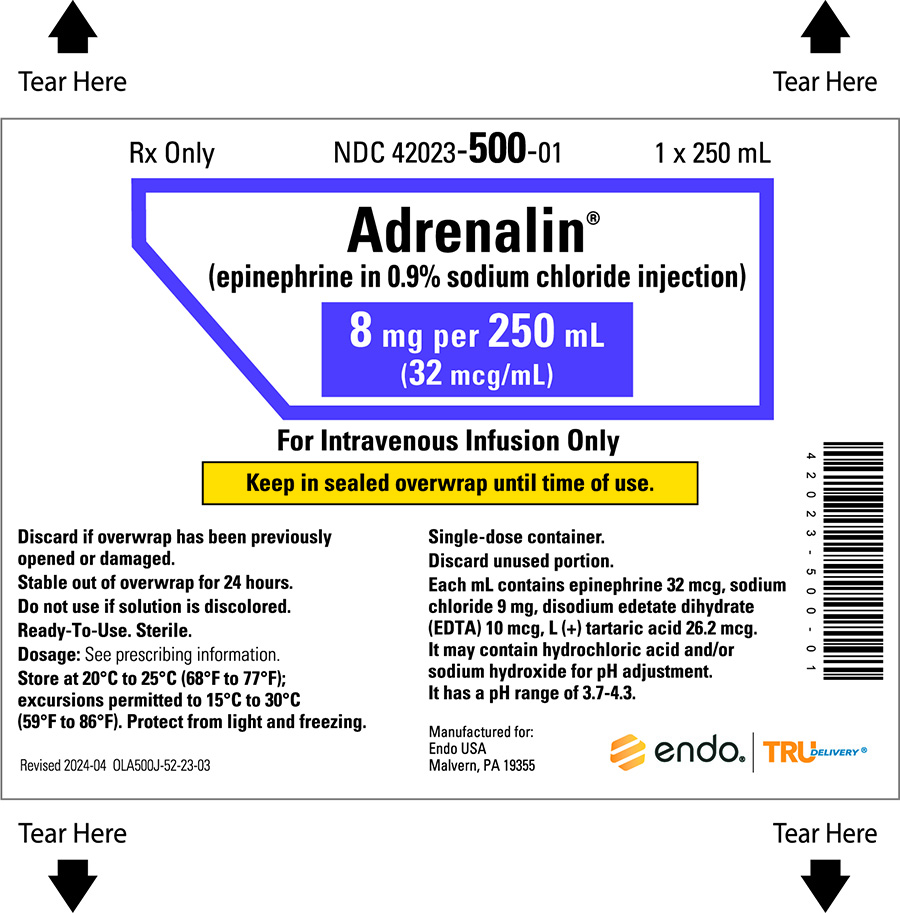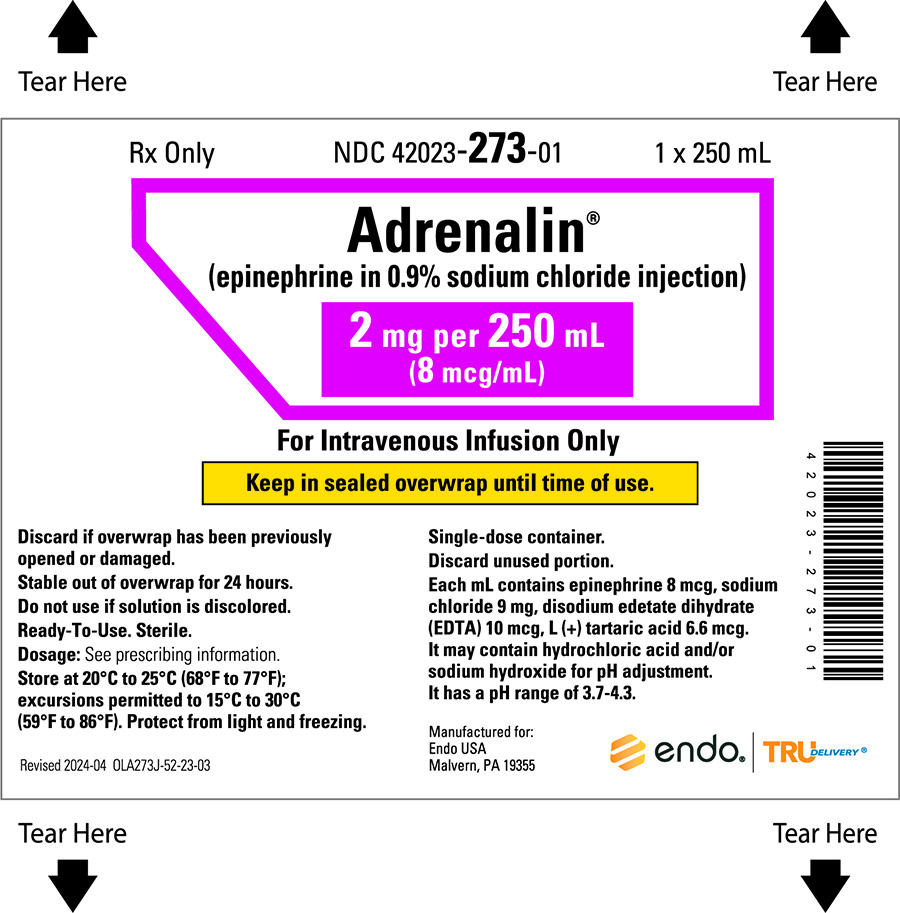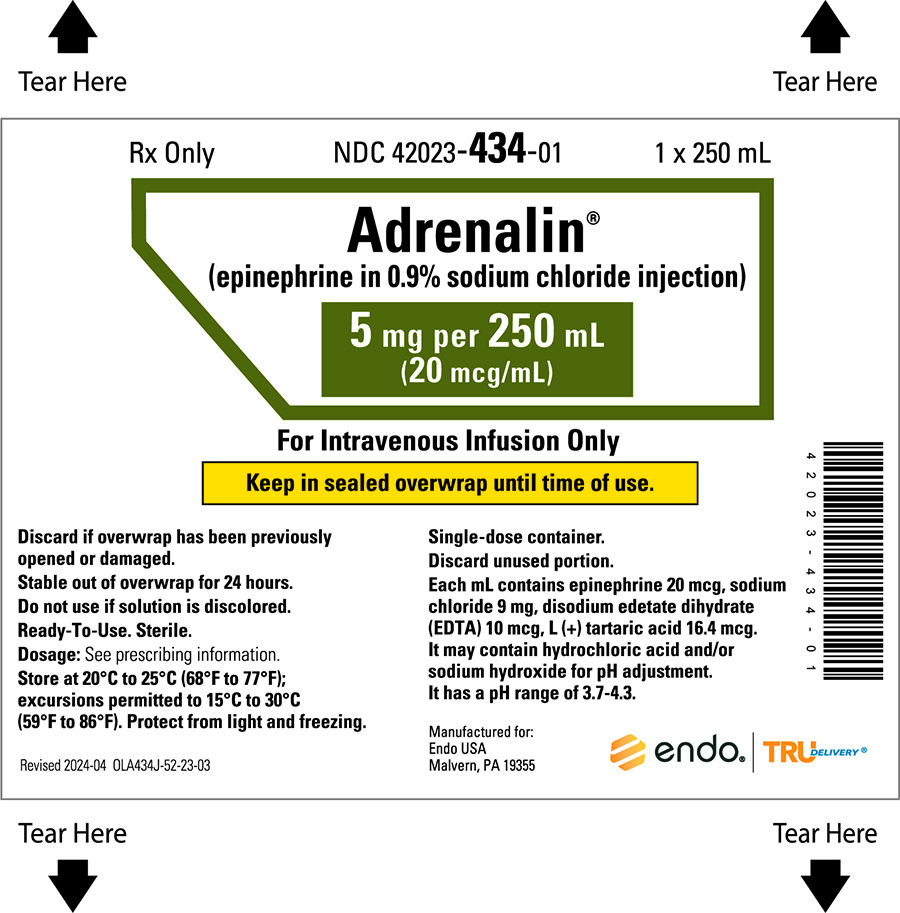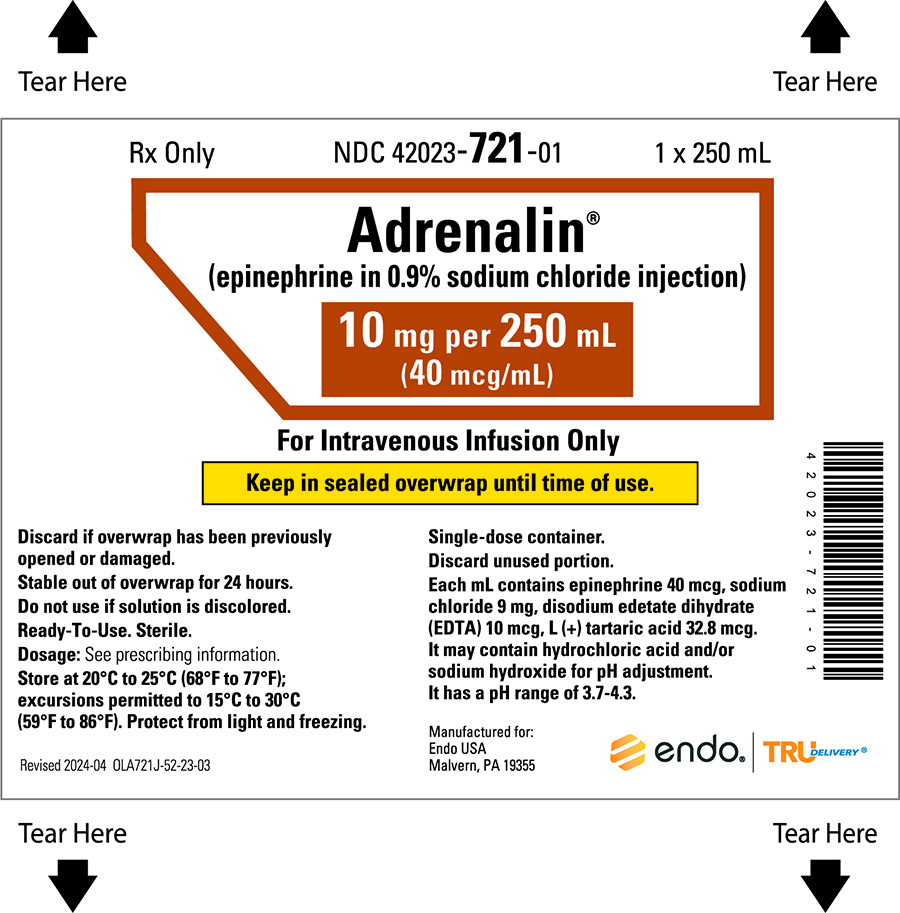 DRUG LABEL: Adrenalin (epinephrine in sodium chloride)
NDC: 42023-315 | Form: INJECTION
Manufacturer: Par Health USA, LLC
Category: prescription | Type: HUMAN PRESCRIPTION DRUG LABEL
Date: 20251015

ACTIVE INGREDIENTS: EPINEPHRINE 16 ug/1 mL
INACTIVE INGREDIENTS: SODIUM CHLORIDE 9 mg/1 mL; TARTARIC ACID 13.1 ug/1 mL; EDETATE DISODIUM 10 ug/1 mL

HIGHLIGHTS OF PRESCRIBING INFORMATION

These highlights do not include all the information needed to use ADRENALIN safely and effectively. See full prescribing information for ADRENALIN.
ADRENALIN (epinephrine in sodium chloride injection), for intravenous use
Initial U.S. Approval: 1939

1. INDICATIONS AND USAGE

Adrenalin® is a non-selective alpha and beta adrenergic agonist indicated to:

- Increase mean arterial blood pressure in adult patients with hypotension associated with septic shock (1.1)

2. DOSAGE AND ADMINISTRATION

- No further dilution prior to infusion is required (2.1)
- Infuse epinephrine into a large vein (2.2)
- Titrate 0.05 mcg/kg/min to 2 mcg/kg/min to achieve desired blood pressure (2.2)
- Wean gradually (2.2)
- See Full Prescribing Information for instructions on administration of the injection.

3. DOSAGE FORMS AND STRENGTHS

- Injection: 250 mL single-dose container with: (3)

- 2 mg epinephrine (8 mcg/mL) in 0.9% sodium chloride

- 4 mg epinephrine (16 mcg/mL) in 0.9% sodium chloride

- 5 mg epinephrine (20 mcg/mL) in 0.9% sodium chloride

- 8 mg epinephrine (32 mcg/mL) in 0.9% sodium chloride

- 10 mg epinephrine (40 mcg/mL) in 0.9% sodium chloride

4. CONTRAINDICATIONS

None (4)

5. WARNINGS AND PRECAUTIONS

- Monitor blood pressure frequently (5.1)
- Increases cardiac output and causes peripheral vasoconstriction (5.2)
- May induce cardiac arrhythmias and myocardial ischemia. (5.3)
- Avoid extravasation into tissues, which can cause local necrosis (5.4)
- May aggravate angina pectoris or produce ventricular arrhythmias (5.5)
- Constricts Renal blood vessels which may result in oliguria or renal impairment (5.5)

6. ADVERSE REACTIONS

Most common adverse reactions to systemically administered epinephrine are headache; anxiety; apprehensiveness; restlessness; tremor; weakness; dizziness; sweating; palpitations; pallor; peripheral coldness; nausea/vomiting; and/or respiratory difficulties. Arrhythmias, including fatal ventricular fibrillation, rapid rises in blood pressure producing cerebral hemorrhage, and angina have occurred. (6)

To report SUSPECTED ADVERSE REACTIONS, contact Endo at 1-800-828-9393 or FDA at 1-800-FDA-1088 or www.fda.gov/medwatch.

7. DRUG INTERACTIONS

- Drugs that counter the pressor effects of epinephrine include alpha blockers, vasodilators such as nitrates, diuretics, antihypertensives and ergot alkaloids. (7.1)
- Drugs that potentiate the effects of epinephrine include sympathomimetics, beta blockers, tricyclic antidepressants, MAO inhibitors, COMT inhibitors, clonidine, doxapram, oxytocin, levothyroxine sodium, and certain antihistamines. (7.2)
- Drugs that increase the arrhythmogenic potential of epinephrine include beta blockers, cyclopropane and halogenated hydrocarbon anesthetics, antihistamines, exogenous thyroid hormones, diuretics, cardiac glycosides and quinidine. Observe for development of cardiac arrhythmias. (7.3)
- Potassium-depleting drugs, including corticosteroids, diuretics, and theophylline, potentiate the hypokalemic effects of epinephrine. (7.4)

8. USE IN SPECIFIC POPULATIONS

- Elderly patients and pregnant women may be at greater risk of developing adverse reactions when epinephrine is administered parenterally (8.1, 8.5)

FULL PRESCRIBING INFORMATION

1. INDICATIONS AND USAGE

1.1. Hypotension associated with Septic Shock

Adrenalin is indicated to increase mean arterial blood pressure in adult patients with hypotension associated with septic shock.

2. DOSAGE AND ADMINISTRATION

2.1. General Considerations

Administration

Adrenalin is a ready to administer product that requires no further dilution prior to infusion. Inspect visually for particulate matter and discoloration prior to administration; solution should be clear and colorless. Do not use if the solution is colored or cloudy, or if it contains particulate matter.

Do not open the aluminum overwrap until time of use. The premixed, ready-to-use infusion bag has a single port for insertion of the infusion set only. This port should not be used to remove content from the bag or add another medication. Once the infusion bag has been connected to the infusion set, it is stable for 24 hours, as long as the bag stays connected to the infusion set. Single dose only.

Discontinuation

When discontinuing the infusion, reduce the flow rate gradually. Avoid abrupt withdrawal. Discard unused portion.

2.2. Hypotension associated with Septic Shock

Whenever possible, give infusions of epinephrine into a large vein. Avoid using a catheter tie-in technique, because the obstruction to blood flow around the tubing may cause stasis and increased local concentration of the drug. Avoid the veins of the leg in elderly patients or in those suffering from occlusive vascular diseases.

To provide hemodynamic support in septic shock associated hypotension in adult patients, the suggested dosing infusion rate of intravenously administered epinephrine is 0.05 mcg/kg/min to 2 mcg/kg/min and is titrated to achieve a desired mean arterial pressure (MAP). The dosage may be adjusted periodically, such as every 10 to 15 minutes, in increments of 0.05 mcg/kg/min to 0.2 mcg/kg/min, to achieve the desired blood pressure goal.

After hemodynamic stabilization, wean incrementally over time, such as by decreasing doses of epinephrine every 10 minutes to determine if the patient can tolerate gradual withdrawal.

3. DOSAGE FORMS AND STRENGTHS

Injection: Epinephrine in sodium chloride is a clear, colorless solution in a ready-to-use, single-dose container available as:

- 2 mg/250mL (8 mcg/mL)
- 4 mg/250mL (16 mcg/mL)
- 5 mg/250mL (20 mcg/mL)
- 8 mg/250mL (32 mcg/mL)
- 10 mg/250mL (40 mcg/mL)

4. CONTRAINDICATIONS

None.

5. WARNINGS AND PRECAUTIONS

5.1. Hypertension

Because individual response to epinephrine may vary significantly, monitor blood pressure frequently and titrate to avoid excessive increases in blood pressure.

Patients receiving monoamine oxidase inhibitors (MAOI) or antidepressants of the triptyline or imipramine types may experience severe, prolonged hypertension when given epinephrine.

5.2. Pulmonary Edema

Epinephrine increases cardiac output and causes peripheral vasoconstriction, which may result in pulmonary edema.

5.3. Cardiac Arrhythmias and Ischemia

Epinephrine may induce cardiac arrhythmias and myocardial ischemia in patients, especially patients suffering from coronary artery disease, or cardiomyopathy.

5.4. Extravasation and Tissue Necrosis with Intravenous Infusion

Avoid extravasation of epinephrine into the tissues, to prevent local necrosis. When Adrenalin is administered intravenously, check the infusion site frequently for free flow. Blanching along the course of the infused vein, sometimes without obvious extravasation, may be attributed to vasa vasorum constriction with increased permeability of the vein wall, permitting some leakage. This also may progress on rare occasions to superficial slough. Hence, if blanching occurs, consider changing the infusion site at intervals to allow the effects of local vasoconstriction to subside.

There is potential for gangrene in a lower extremity when infusions of catecholamine are given in an ankle vein.

Antidote for Extravasation Ischemia: To prevent sloughing and necrosis in areas in which extravasation has taken place, infiltrate the area with 10 mL to 15 mL of saline solution containing from 5 mg to 10 mg of phentolamine, an adrenergic blocking agent. Use a syringe with a fine hypodermic needle, with the solution being infiltrated liberally throughout the area, which is easily identified by its cold, hard, and pallid appearance. Sympathetic blockade with phentolamine causes immediate and conspicuous local hyperemic changes if the area is infiltrated within 12 hours.

5.5. Renal Impairment

Epinephrine constricts renal blood vessels, which may result in oliguria or renal impairment.

6. ADVERSE REACTIONS

The following adverse reactions are discussed elsewhere in labeling:

- Hypertension [see Warnings and Precautions (5.1)]
- Pulmonary Edema [see Warnings and Precautions (5.2)]
- Cardiac Arrhythmias and Ischemia [see Warnings and Precautions (5.3)]
- Extravasation and Tissue Necrosis with Intravenous Infusion [see Warnings and Precautions (5.4)]
- Renal Impairment [see Warnings and Precautions (5.5)]

The following adverse reactions associated with the infusion of epinephrine were identified in the literature. Because these reactions are reported voluntarily from a population of uncertain size, it is not always possible to estimate their frequency reliably or to establish a causal relationship to drug exposure.

Cardiovascular disorders: tachycardia, supraventricular tachycardia, ventricular arrhythmias, myocardial ischemia, myocardial infarction, limb ischemia, pulmonary edema

Gastrointestinal disorders: Nausea, vomiting

General disorders and administrative site conditions: Chest pain, extravasation

Metabolic: hypoglycemia, hyperglycemia, insulin resistance, hypokalemia, lactic acidosis

Nervous system disorders: Headache, nervousness, paresthesia, tremor, stroke, central nervous system bleeding

Psychiatric disorders: Excitability

Renal disorders: Renal insufficiency

Respiratory: Pulmonary edema, rales

Skin and subcutaneous tissue disorders: Diaphoresis, pallor, piloerection, skin blanching, skin necrosis with extravasation

7. DRUG INTERACTIONS

7.1. Drugs Antagonizing Pressor Effects of Epinephrine

- α-blockers, such as phentolamine
- Vasodilators, such as nitrates
- Diuretics
- Antihypertensives
- Ergot alkaloids
- Phenothiazine antipsychotics

7.2. Drugs Potentiating Pressor Effects of Epinephrine

- Sympathomimetics
- β-blockers, such as propranolol
- Tricyclic anti-depressants
- Monoamine oxidase (MAO) inhibitors
- Catechol-O-methyl transferase (COMT) inhibitors, such as entacapone
- Clonidine
- Doxapram
- Oxytocin

7.3. Drugs Potentiating Arrhythmogenic Effects of Epinephrine

Patients who are concomitantly receiving any of the following drugs should be observed carefully for the development of cardiac arrhythmias [see Warnings and Precautions (5.5) and Adverse Reactions (6)].

- β-blockers, such as propranolol
- Cyclopropane or halogenated hydrocarbon anesthetics, such as halothane
- Antihistamines
- Thyroid hormones
- Diuretics
- Cardiac glycosides, such as digitalis glycosides
- Quinidine

7.4. Drugs Potentiating Hypokalemic Effects of Epinephrine

- Potassium depleting diuretics
- Corticosteroids
- Theophylline

8. USE IN SPECIFIC POPULATIONS

8.1. Pregnancy

Risk Summary

Limited published data on epinephrine use in pregnant women are not sufficient to determine a drug-associated risk of major birth defects or miscarriage. However, there are risks to the mother and fetus associated with epinephrine use during labor or delivery and risks due to untreated hypotension associated with septic shock (see Clinical Considerations). In animal reproduction studies, epinephrine demonstrated adverse developmental effects when administered to pregnant rabbits (gastroschisis), mice (teratogenic effects, embryonic lethality, and delayed skeletal ossification), and hamsters (embryonic lethality and delayed skeletal ossification) during organogenesis at doses approximately 15 times, 3 times and 2 times, respectively, the maximum recommended daily dose (see Data).

The estimated background risk of major birth defects and miscarriage for the indicated population is unknown. All pregnancies have a background risk of birth defect, loss, or other adverse outcomes. In the United States general population, the estimated background risk of major birth defects and miscarriage in clinically recognized pregnancies is 2-4% and 15-20%, respectively.

Clinical Considerations

Disease-associated maternal and/or embryo/fetal risk

Hypotension associated with septic shock is a medical emergency in pregnancy which can be fatal if left untreated. Delaying treatment in pregnant women with hypotension associated with septic shock may increase the risk of maternal and fetal morbidity and mortality. Do not withhold life-sustaining therapy for a pregnant woman.

Labor or Delivery

Epinephrine usually inhibits spontaneous, or oxytocin induced contractions of the pregnant human uterus and may delay the second stage of labor. Avoid epinephrine during the second stage of labor. In dosage sufficient to reduce uterine contractions, the drug may cause a prolonged period of uterine atony with hemorrhage. Avoid epinephrine in obstetrics when maternal blood pressure exceeds 130/80 mmHg.

Although epinephrine may improve maternal hypotension associated with septic shock, it may result in uterine vasoconstriction, decreased uterine blood flow, and fetal anoxia.

Data

Animal Data

In an embryofetal development study with pregnant rabbits dosed during the period of organogenesis (on days 3 to 5, 6 to 7 or 7 to 9 of gestation), epinephrine caused teratogenic effects (including gastroschisis) at doses approximately 15 times the maximum recommended intramuscular, subcutaneous, or intravenous dose (on a mg/m^2 basis at a maternal subcutaneous dose of 1.2 mg/kg/day for two to three days). Animals treated on days 6 to 7 had decreased number of implantations.

In an embryofetal development study, pregnant mice were administered epinephrine (0.1 to 10 mg/kg/day) on Gestation Days 6 to 15. Teratogenic effects, embryonic lethality, and delays in skeletal ossification were observed at approximately 3 times the maximum recommended intramuscular, subcutaneous, or intravenous dose (on a mg/m^2 basis at maternal subcutaneous dose of 1 mg/kg/day for 10 days). These effects were not seen in mice at approximately 2 times the maximum recommended daily intramuscular or subcutaneous dose (on a mg/m^2 basis at a subcutaneous maternal dose of 0.5 mg/kg/day for 10 days).

In an embryofetal development study with pregnant hamsters dosed during the period of organogenesis from gestation days 7 to 10, epinephrine produced reductions in litter size and delayed skeletal ossification at doses approximately 2 times the maximum recommended intramuscular, subcutaneous, or intravenous dose (on a mg/m^2 basis at a maternal subcutaneous dose of 0.5 mg/kg/day).

8.2. Lactation

Risk Summary

There is no information regarding the presence of epinephrine in human milk or the effects of epinephrine on the breastfed infant or on milk production. However, due to its poor oral bioavailability and short half-life, epinephrine exposure is expected to be very low in the breastfed infant. The lack of clinical data during lactation precludes a clear determination of the risk of epinephrine to a breastfed infant.

8.4. Pediatric Use

Safety and effectiveness of epinephrine in pediatric patients with septic shock have not been established.

8.5. Geriatric Use

Clinical studies of epinephrine for the treatment of hypotension associated with septic shock did not include sufficient numbers of subjects aged 65 and over to determine whether they respond differently from younger subjects. Other reported clinical experience has not identified differences in responses between the elderly and younger patients. In general, dose selection for an elderly patient should be cautious, usually starting at the low end of the dosing range, reflecting the greater frequency of decreased hepatic, renal, or cardiac function, and of concomitant disease or other drug therapy.

10. OVERDOSAGE

Overdosage of epinephrine may produce extremely elevated arterial pressure, which may result in cerebrovascular hemorrhage, particularly in elderly patients. Overdosage may also result in pulmonary edema because of peripheral vascular constriction together with cardiac stimulation. Epinephrine overdosage can also cause transient bradycardia followed by tachycardia and these may be accompanied by potentially fatal cardiac arrhythmias. Premature ventricular contractions may appear within one minute after injection and may be followed by multifocal ventricular tachycardia (prefibrillation rhythm). Subsidence of the ventricular effects may be followed by atrial tachycardia and occasionally by atrioventricular block. Myocardial ischemia and infarction, cardiomyopathy, extreme pallor and coldness of the skin, metabolic acidosis due to elevated blood lactic acid levels, and renal insufficiency and failure have also been reported.

Epinephrine is rapidly inactivated in the body and treatment following overdose with epinephrine is primarily supportive. Treatment of pulmonary edema consists of a rapidly acting alpha- adrenergic blocking drug (such as phentolamine mesylate) and respiratory support. Treatment of arrhythmias consists of administration of a beta-adrenergic blocking drug (such as propranolol). If necessary, pressor effects may be counteracted by rapidly acting vasodilators (such as nitrates) or α-adrenergic blocking drugs. If prolonged hypotension follows such measures, it may be necessary to administer another pressor drug.

11. DESCRIPTION

Adrenalin (epinephrine in sodium chloride injection) is a sympathomimetic catecholamine. The chemical name of epinephrine is: 1,2- Benzenediol, 4-[(1R)-1-hydroxy-2-(methylamino)ethyl]-, or (-)-3,4-Dihydroxy-α-[2- (methylamino)ethyl]benzyl alcohol.

The chemical structure of epinephrine is:

The molecular weight of epinephrine is 183.2.

Epinephrine solution deteriorates rapidly on exposure to air or light, turning pink from oxidation to adrenochrome and brown from the formation of melanin.

Adrenalin (epinephrine in sodium chloride injection) is a clear, colorless, sterile solution administered by intravenous infusion, supplied in a 250 mL infusion bag. It is provided in five (5) ready-to-use concentrations containing:

Ingredient | Concentration
Ingredient | 8 mcg/mL | 16 mcg/mL | 20 mcg/mL | 32 mcg/mL | 40 mcg/mL
Epinephrine, USP | 8 mcg | 16 mcg | 20 mcg | 32 mcg | 40 mcg
Sodium chloride, USP | 9 mg | 9 mg | 9 mg | 9 mg | 9 mg
Disodium Edetate Dihydrate (EDTA), USP | 10 mcg | 10 mcg | 10 mcg | 10 mcg | 10 mcg
L (+) Tartaric Acid, NF | 6.6 mcg | 13.1 mcg | 16.4 mcg | 26.2 mcg | 32.8 mcg

It may contain hydrochloric acid and/or sodium hydroxide for pH adjustment. It has a pH range of 3.7 - 4.3. The headspace in the containers has been displaced with nitrogen gas.

12. CLINICAL PHARMACOLOGY

12.1. Mechanism of Action

Epinephrine acts on both alpha and beta-adrenergic receptors. The mechanism of the rise in blood pressure is 3-fold: a direct myocardial stimulation that increases the strength of ventricular contraction (positive inotropic action), an increased heart rate (positive chronotropic action), and peripheral vasoconstriction.

12.2. Pharmacodynamics

Intravenous use for hypotension associated with septic shock

Following intravenous administration of epinephrine, increases in systolic blood pressure and heart rate are observed. Decreases in systemic vascular resistance and diastolic blood pressure are observed at low doses of epinephrine because of β2-mediated vasodilation, but are overtaken by α1-mediated peripheral vasoconstriction at higher doses leading to increase in diastolic blood pressure. The onset of blood pressure increase following an intravenous dose of epinephrine is < 5 minutes and the time to offset blood pressure response occurs within 15 minutes. Most vascular beds are constricted including renal, splanchnic, mucosal and skin.

Epinephrine causes mydriasis when administered parenterally.

12.3. Pharmacokinetics

Following intravenous injection, epinephrine is rapidly cleared from the plasma with an effective half-life of < 5 minutes. A pharmacokinetic steady state following continuous intravenous infusion is achieved within 10-15 minutes. In patients with septic shock, epinephrine displays dose-proportional pharmacokinetics in the infusion dose range of 0.03 to 1.7 mcg/kg/min.

Epinephrine is extensively metabolized with only a small amount excreted unchanged.

Epinephrine is rapidly degraded to vanillylmandelic acid, an inactive metabolite, by monoamine oxidase and catechol-O-methyltransferase that are abundantly expressed in the liver, kidneys and other extraneuronal tissues. The tissues with the highest contribution to removal of circulating exogenous epinephrine are the liver (32%), kidneys (25%), skeletal muscle (20%), and mesenteric organs (12%).

Specific Populations

Elderly

In a pharmacokinetic study of 45-minute epinephrine infusions given to healthy men aged 20 to 25 years and healthy men aged 60 to 65 years, the mean plasma metabolic clearance rate of epinephrine at steady state was greater among the older men (144.8 versus 78 mL/kg/min for a 0.0143 mcg/kg/min infusion).

Body Weight

Body weight has been found to influence epinephrine pharmacokinetics. Higher body weight was associated with a higher plasma epinephrine clearance and a lower concentration plateau.

13. NONCLINICAL TOXICOLOGY

13.1. Carcinogenesis, Mutagenesis, Impairment of Fertility

Long-term studies to evaluate the carcinogenic potential of epinephrine have not been conducted.

Epinephrine and other catecholamines have been shown to have mutagenic potential in vitro.

Epinephrine was positive in the Salmonella bacterial reverse mutation assay, positive in the mouse lymphoma assay, and negative in the in vivo micronucleus assay. Epinephrine is an oxidative mutagen based on the E. coli WP2 Mutoxitest bacterial reverse mutation assay. This should not prevent the use of epinephrine under the conditions noted under Indications and Usage (1).

The potential for epinephrine to impair reproductive performance has not been evaluated, but epinephrine has been shown to decrease implantation in female rabbits dosed subcutaneously with 1.2 mg/kg/day (15-fold the highest human intramuscular or subcutaneous daily dose) during gestation days 3 to 9.

16. HOW SUPPLIED/STORAGE AND HANDLING

Adrenalin (epinephrine in sodium chloride injection) is supplied as a clear, colorless sterile solution in a single-dose 250 mL non-PVC infusion bag with a single function connector system consisting of a port and cap, packaged individually in an aluminum overwrap with an oxygen scavenger.

Supplied as:

Unit of Sale | Strength | Pack Factor
NDC 42023-273-10 | 2 mg/250 mL (8 mcg/mL) | 10 units
NDC 42023-315-10 | 4 mg/250 mL (16 mcg/mL) | 10 units
NDC 42023-434-10 | 5 mg/250 mL (20 mcg/mL) | 10 units
NDC 42023-500-10 | 8 mg/250 mL (32 mcg/mL) | 10 units
NDC 42023-721-10 | 10 mg/250 mL (40 mcg/mL) | 10 units

Store between 20°C to 25°C (68°F to 77°F) [See USP Controlled Room Temperature]. Epinephrine is light sensitive. Protect from light and freezing.

Keep in foil overwrap until ready to use. Discard after 24 hours of opening overwrap.

Manufactured for:

Endo USA

Malvern, PA 19355

© 2024 Endo, Inc. or one of its affiliates.

Revised: 04/2024